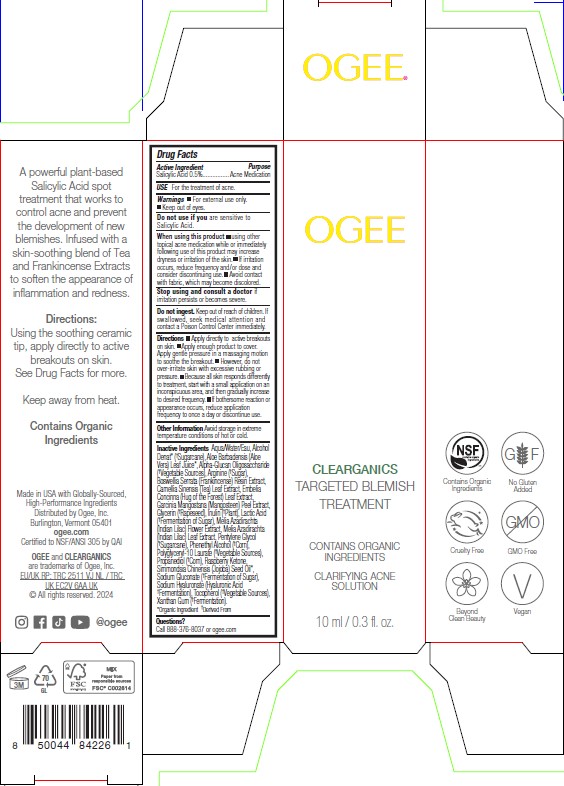 DRUG LABEL: OGEE CLEARGANICS TARGETED BLEMISH TREATMENT
NDC: 84261-154 | Form: SOLUTION
Manufacturer: Ogee Inc
Category: otc | Type: HUMAN OTC DRUG LABEL
Date: 20251126

ACTIVE INGREDIENTS: SALICYLIC ACID 0.5 g/100 mL
INACTIVE INGREDIENTS: ALCOHOL; WATER; POLYGLYCERYL-10 LAURATE; ARGININE; TEA LEAF; PHENYLETHYL ALCOHOL; INULIN; AZADIRACHTA INDICA FLOWER; LACTIC ACID; GARCINIA MANGOSTANA FRUIT RIND; GLYCERIN; 4-(P-HYDROXYPHENYL)-2-BUTANONE; INDIAN FRANKINCENSE; PENTYLENE GLYCOL; PROPANEDIOL; XANTHAN GUM; ALOE VERA LEAF; .ALPHA.-GLUCAN OLIGOSACCHARIDE; HYALURONATE SODIUM; AZADIRACHTA INDICA LEAF; JOJOBA OIL; SODIUM GLUCONATE; EMBELIA RIBES FRUIT; TOCOPHEROL

OGEE CLEARGANICS TARGETED BLEMISH TREATMENT

Active Ingredient

Salicylic Acid 0.5%

Purpose

Acne Medication

Uses

For the treatment of acne.

Warnings

■For external use only.

■Keep out of eyes.

Do not use if you are sensitive to Salicylic Acid.

When using this product ■ using other topical acne medication while or immediately following use of this product may increase dryness or irritation of the skin. ■ If irritation occurs, reduce frequency and/or dose and consider discontinuing use. ■ Avoid contact with fabric, which may become discolored.

Stop using and consult a doctor if irritation persists or becomes severe.

Do not ingest. Keep out of reach of children. If swallowed, seek medical attention and contact a Poison Control Center immediately.

Keep out of reach of children. If swallowed, seek medical attention and contact a Poison Control Center immediately.

Directions

■ Apply directly to active breakouts on skin. ■ Apply enough product to cover. Apply gentle pressure in a massaging motion to soothe the breakout. ■ However, do not over-irritate skin with excessive rubbing or pressure. ■ Because all skin responds differently to treatment, start with a small application on an inconspicuous area, and then gradually increase to desired frequency. ■ If bothersome reaction or appearance occurs, reduce application frequency to once a day or discontinue use.

Other Information

Avoid storage in extreme temperature conditions of hot or cold.

Inactive ingredients

Aqua/Water/Eau, Alcohol Denat* (†Sugarcane), Aloe Barbadensis (Aloe Vera) Leaf Juice*, Alpha-Glucan Oligosaccharide (†Vegetable Sources), Arginine (†Sugar), Boswellia Serrata (Frankincense) Resin Extract, Camellia Sinensis (Tea) Leaf Extract, Embelia Concinna (Hug of the Forest) Leaf Extract, Garcinia Mangostana (Mangosteen) Peel Extract, Glycerin (†Rapeseed), Inulin (†Plant), Lactic Acid (†Fermentation of Sugar), Melia Azadirachta (Indian Lilac) Flower Extract, Melia Azadirachta (Indian Lilac) Leaf Extract, Pentylene Glycol (†Sugarcane), Phenethyl Alcohol (†Corn), Polyglyceryl-10 Laurate (†Vegetable Sources), Propanediol (†Corn), Raspberry Ketone, Simmondsia Chinensis (Jojoba) Seed Oil*, Sodium Gluconate (†Fermentation of Sugar), Sodium Hyaluronate (Hyaluronic Acid †Fermentation), Tocopherol (†Vegetable Sources), Xanthan Gum (†Fermentation).
*Organic Ingredient †Derived From

Questions

Call 888-376-8037 or ogee.com

Principal Display Panel

OGEE

CLEARGANICS

TARGETED BLEMISH

TREATMENT

CONTAINS ORGANIC

INGREDIENTS

CLARIFYING ACNE

SOLUTION

10 ml / 0.3 fl. oz.

A powerful plant-based
Salicylic Acid spot
treatment that works to
control acne and prevent
the development of new
blemishes. Infused with a
skin-soothing blend of Tea
and Frankincense Extracts
to soften the appearance of
inflammation and redness.
Directions:
Using the soothing ceramic
tip, apply directly to active
breakouts on skin.
See Drug Facts for more.
Keep away from heat.
Contains Organic
Ingredients

Made in USA with Globally-Sourced,
High-Performance Ingredients
Distributed by Ogee, Inc.
Burlington, Vermont 05401
ogee.com
Certified to NSF/ANSI 305 by QAI
OGEE and CLEARGANICS
are trademarks of Ogee, Inc.
EU/UK RP: TRC 2511 VJ NL / TRC
UK EC2V 6AA UK
© All rights reserved. 2024

Contains Organic
Ingredients
Cruelty Free
Beyond
Clean Beauty
No Gluten
Added
GMO Free
Vegan